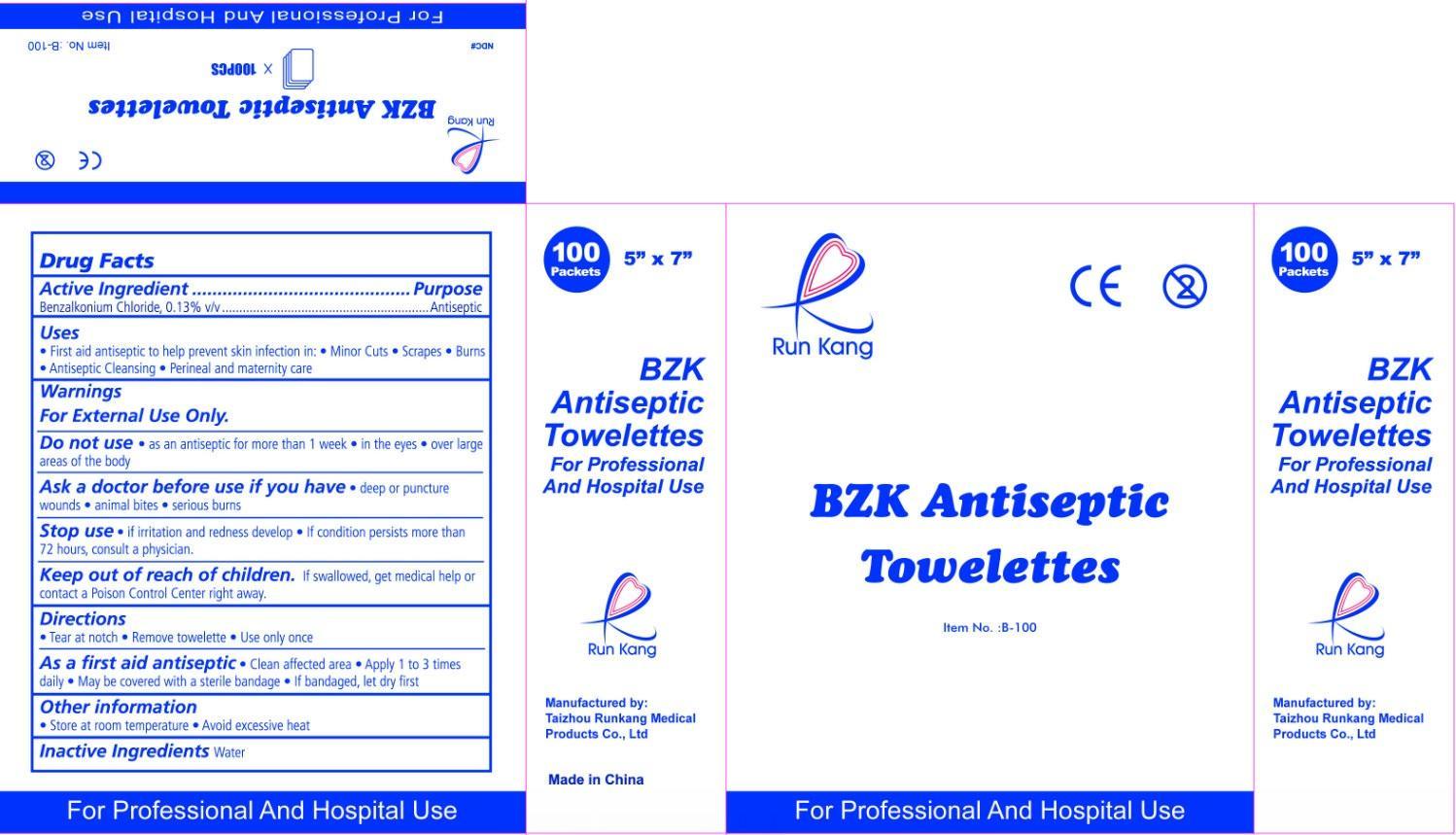 DRUG LABEL: Run Kang BZK Antiseptic Towelettes
                
NDC: 57775-000 | Form: LIQUID
Manufacturer: Taizhou Runkang Medical Products Co.,Ltd.
Category: otc | Type: HUMAN OTC DRUG LABEL
Date: 20130408

ACTIVE INGREDIENTS: BENZALKONIUM CHLORIDE 0.13 g/100 g
INACTIVE INGREDIENTS: WATER

Run Kang BZK Antiseptic Towelettes

Active Ingredient

Benzalkonium Chloride, 0.13% v/v

Purpose

Antiseptic

Uses

- First aid antiseptic to help prevent skin infection in:
- Minor cuts
- Scrapes
- Burns
- Antiseptic Cleansing
- Perineal and maternity care

Warnings

For External Use Only.

Do not use

- as an antiseptic for more than 1 week - in the eyes - over large areas of the body

Ask a doctor before use if you have

- deep or puncture wounds - animal bites - serious burns

Stop use

- If irritation and redness develop - if condition persists more than 72 hours, consult a physician.

Keep out of reach of children.

If swallowed, get medical help or contact a Poison Control Center right away.

Directions

- Tear at notch - Remove towelette - Use only once

As a first aid antiseptic

- Clean affected area - Apply 1 to 3 times daily - May be covered with a sterile bandage - If bandaged, let dry first

Other information

- Store at room temperature
- Avoid excessive heat

Inactive Ingredients

Water

For Professional And Hospital Use

100 Packets 5" x 7" BZK Antiseptic Toweletted For Professional And Hospital Use Run Kang Manufactured by: Taizhou Runkang Medical Products Co., Ltd. Made in China

PACKAGE LABEL

Run Kang BZK Antiseptic Towelettes Item No. :B-100 For Professional And Hospital Use